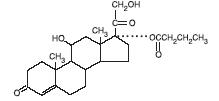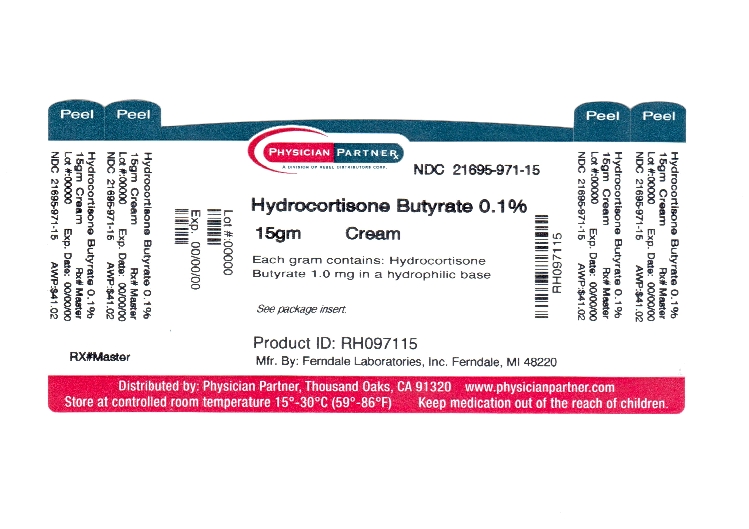 DRUG LABEL: Hydrocortisone Butyrate
NDC: 21695-971 | Form: CREAM
Manufacturer: Rebel Distributors Corp
Category: prescription | Type: HUMAN PRESCRIPTION DRUG LABEL
Date: 20110913

ACTIVE INGREDIENTS: HYDROCORTISONE BUTYRATE 1.0 mg/1 g
INACTIVE INGREDIENTS: CETETH-20; CETOSTEARYL ALCOHOL; LIGHT MINERAL OIL; PROPYLPARABEN; BUTYLPARABEN; CITRIC ACID MONOHYDRATE; SODIUM CITRATE; WATER

Hydrocortisone Butyrate Cream, USP, 0.1%
For Dermatological Use Only

DESCRIPTION

Hydrocortisone Butyrate Cream USP, 0.1% contains the topical corticosteroid hydrocortisone butyrate, a non-fluorinated hydrocortisone ester. It has the chemical name: pregn-4-ene-3,20-dione, 11,21 - dihydroxy-17-[(1-oxobutyl)oxy]-, (11β-); the molecular formula: C25H36O6; the molecular weight: 432.54; and the CAS registry number: 13609-67-1.

Its structural formula is:

Each gram of hydrocortisone butyrate cream USP, 0.1% contains 1.0 mg of hydrocortisone butyrate in a hydrophilic base consisting of cetostearyl alcohol, ceteth-20, mineral oil, white petrolatum, citric acid, sodium citrate, propylparaben and butylparaben (preservatives) and purified water.

CLINICAL PHARMACOLOGY

Topical corticosteroids share anti-inflammatory, anti-pruritic and vasoconstrictive actions. The mechanism of anti-inflammatory activity of the topical corticosteroids is unclear. Various laboratory methods, including vasoconstrictor assays, are used to compare and predict potencies and/or clinical efficacies of the topical corticosteroids. There is some evidence to suggest that a recognizable correlation exists between vasoconstrictor potency and therapeutic efficacy in man.

PHARMACOKINETICS

The extent of percutaneous absorption of topical corticosteroids is determined by many factors including the vehicle, the integrity of the epidermal barrier, and the use of occlusive dressings.

Topical corticosteroids can be absorbed from normal intact skin. Inflammation and/or other disease processes in the skin increase percutaneous absorption. Occlusive dressings substantially increase the percutaneous absorption of topical corticosteroids.

Thus, occlusive dressings may be a valuable therapeutic adjunct for treatment of resistant dermatoses.

(See DOSAGE AND ADMINISTRATION.)

Once absorbed through the skin, topical corticosteroids are handled through pharmacokinetic pathways similar to systemically administered corticosteroids. Corticosteroids are bound to plasma proteins in varying degrees. Corticosteroids are metabolized primarily in the liver and are then excreted by the kidneys. Some of the topical corticosteroids and their metabolites are also excreted into the bile.

INDICATIONS AND USAGE

Hydrocortisone butyrate cream USP, 0.1% is indicated for the relief of the inflammatory and pruritic manifestations of corticosteroid-responsive dermatoses.

CONTRAINDICATIONS

Topical corticosteroids are contraindicated in those patients with a history of hypersensitivity to any of the components of the preparation.

PRECAUTIONS

General

Systemic absorption of topical corticosteroids has produced reversible hypothalamic-pituitary-adrenal (HPA) axis suppression, manifestations of Cushing's syndrome, hyperglycemia, and glucosuria in some patients. Conditions which augment systemic absorption include the application of the more potent steroids, use over large surface areas, prolonged use, and the addition of occlusive dressings.

Therefore, patients receiving a large dose of a potent topical steroid applied to a large surface area or under an occlusive dressing should be evaluated periodically for evidence of HPA axis suppression by using the urinary free cortisol and ACTH stimulation tests.

If HPA axis suppression is noted, an attempt should be made to withdraw the drug, to reduce the frequency of application, or to substitute a less potent steroid.

Recovery of HPA axis function is generally prompt and complete upon discontinuation of the drug.

Infrequently, signs and symptoms of steroid withdrawal may occur, requiring supplemental systemic corticosteroids.

Children may absorb proportionally larger amounts of topical corticosteroids and thus be more susceptible to systemic toxicity.

(See PRECAUTIONS - PEDIATRIC USE).

If irritation develops, topical corticosteroids should be discontinued and appropriate therapy instituted.

In the presence of dermatological infections, the use of an appropriate antifungal or antibacterial agent should be instituted. If a favorable response does not occur promptly, the corticosteroid should be discontinued until the infection has been adequately controlled.

Information for the Patient

Patients using topical corticosteroids should receive the following information and instructions:

1. This medication is to be used as directed by the physician. It is for external use only. Avoid contact with the eyes.

2. Patients should be advised not to use this medication for any disorder other than for which it was prescribed.

3. The treated skin area should not be bandaged or otherwise covered or wrapped as to be occlusive unless directed by the physician.

4. Patients should report any signs of local adverse reactions especially under occlusive dressing.

5. Parents of pediatric patients should be advised not to use tight-fitting diapers or plastic pants on a child being treated in the diaper area, as these garments may constitute occlusive dressings.

Laboratory Tests

The following tests may be helpful in evaluating the HPA axis suppression:

Urinary free cortisol test

ACTH stimulation test

Carcinogenesis, Mutagenesis, and Impairment of Fertility

Long-term animal studies have not been performed to evaluate the carcinogenic potential or the effect on fertility of topical corticosteroids.

Studies to determine mutagenicity with prednisolone and hydrocortisone have revealed negative results.

Pregnancy Category C

Corticosteroids are generally teratogenic in laboratory animals when administered systemically at relatively low dosage levels. The more potent corticosteroids have been shown to be teratogenic after dermal application in laboratory animals. There are no adequate and well-controlled studies in pregnant women on teratogenic effects from topically applied corticosteroids. Therefore, topical corticosteroids should be used during pregnancy only if the potential benefit justifies the potential risk to the fetus.

Drugs of this class should not be used extensively on pregnant patients, in large amounts, or for prolonged periods of time.

Nursing Mothers

It is not known whether topical administration of corticosteroids could result in sufficient systemic absorption to produce detectable quantities in breast milk. Systemically administered corticosteroids are secreted into breast milk, in quantities not likely to have a deleterious effect on the infant. Nevertheless, caution should be exercised when topical corticosteroids are administered to a nursing woman.

Pediatric Use

Pediatric patients may demonstrate greater susceptibility to topical corticosteroid-induced HPA axis suppression and Cushing's syndrome than mature patients because of a larger skin surface area to body weight ratio.

Hypothalamic-pituitary-adrenal (HPA) axis suppression, Cushing's syndrome, and intracranial hypertension have been reported in children receiving topical corticosteroids.

Manifestations of adrenal suppression in children include linear growth retardation, delayed weight gain, low plasma cortisol levels, and absence of response to ACTH stimulation. Manifestations of intracranial hypertension include bulging fontanelles, headaches, and bilateral papilledema.

Administration of topical corticosteroids to children should be limited to the least amount compatible with an effective therapeutic regimen. Chronic corticosteroid therapy may interfere with the growth and development of children.

ADVERSE REACTIONS

The following local adverse reactions are reported infrequently with topical corticosteroids but may occur more frequently with the use of occlusive dressings. These reactions are listed in an approximate decreasing order of occurrence: burning, itching, irritation, dryness, folliculitis, hypertrichosis, acneiform eruptions, hypopigmentation, perioral dermatitis, allergic contact dermatitis, maceration of the skin, secondary infection, skin atrophy, striae, miliaria.

OVERDOSAGE

Topically applied corticosteroids can be absorbed in sufficient amounts to produce systemic effects. (See PRECAUTIONS.)

DOSAGE AND ADMINISTRATION

Hydrocortisone butyrate cream USP, 0.1% should be applied to the affected area as a thin film two or three times daily depending on the severity of the condition. Occlusive dressings may be used for the management of psoriasis or recalcitrant conditions.

If an infection develops, the use of occlusive dressings should be discontinued and appropriate antimicrobial therapy instituted.

HOW SUPPLIED

Hydrocortisone Butyrate Cream, USP, 0.1% is supplied in tubes containing:

15 g NDC 21695-971-15

STORAGE

Store at controlled temperature between 59° - 77°F (15° - 25°C).

Rx Only

Manufactured for Rouses Point

Pharmaceuticals, LLC

Cranford, NJ 07016

By Ferndale Laboratories, Inc.

Ferndale, MI 48220

127F000

Rev 11/08

Repackaged by:

Rebel Distributors Corp

Thousand Oaks, CA 91320